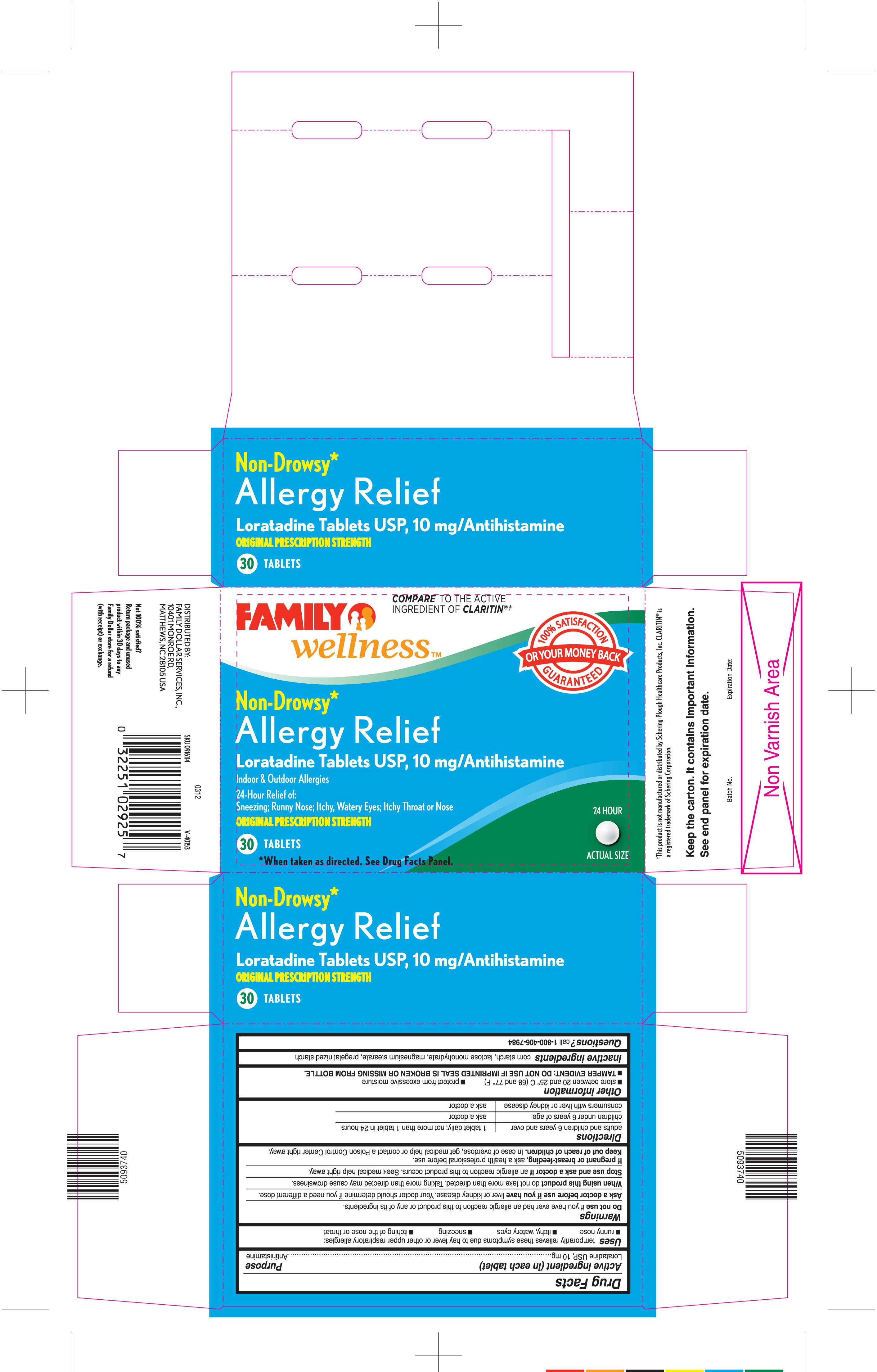 DRUG LABEL: Loratadine
NDC: 55319-526 | Form: TABLET
Manufacturer: Family Dollar Services, Inc.
Category: otc | Type: HUMAN OTC DRUG LABEL
Date: 20130313

ACTIVE INGREDIENTS: LORATADINE 10 mg/1 1
INACTIVE INGREDIENTS: STARCH, CORN; LACTOSE MONOHYDRATE; MAGNESIUM STEARATE; STARCH, PREGELATINIZED CORN

Drug Facts

ACTIVE INGREDIENT (IN EACH TABLET)

Loratadine USP, 10 mg

PURPOSE

Antihistamine

USES

Temporarily relieves these symptoms due to hay fever or other upper respiratory allergies:

- runny nose
- itchy, watery eyes
- sneezing
- itching of the nose or throat

WARNINGS

Do not use

If you have ever had an allergic reaction to this product or any of its ingredients.

Ask a doctor before use if you have

Liver or kidney disease. Your doctor should determine if you need a different dose.

When using this product

Do not take more than directed. Taking more than directed may cause drowsiness.

Stop use and ask a doctor if

An allergic reaction to this product occurs. Seek medical help right away.

If pregnant or breast-feeding

Ask a health professional before use.

Keep out of reach of children.

In case of overdose, get medical help or contact a Poison Control Center right away.

DIRECTIONS

adults and children 6 years and over | 1 tablet daily; not more than 1 tablet in 24 hours
children under 6 years of age | ask a doctor
consumers with liver or kidney disease | ask a doctor

OTHER INFORMATION

- store between 20 and 25° C (68 and 77° F)
- protect from excessive moisture
- TAMPER EVIDENT: DO NOT USE IF IMPRINTED SEAL IS BROKEN OR MISSING FROM BOTTLE.

INACTIVE INGREDIENTS

Corn starch, lactose monohydrate, magnesium stearate, pregelatinized starch

QUESTIONS?

Call 1-800-406-7984

PRINCIPAL DISPLAY PANEL

FAMILY wellness™

COMPARE TO THE ACTIVE INGREDIENT OF CLARITIN®†

Non-Drowsy*

Allergy Relief

Loratadine Tablets USP, 10 mg/Antihistamine

Indoor & Outdoor Allergies

24-Hour Relief of:

Sneezing; Runny Nose; Itchy, Watery Eyes; Itchy Throat or Nose

ORIGINAL PRESCRIPTION STRENGTH

24 HOUR

30 TABLETS

* When taken as directed.

See Drug Facts Panel.

DISTRIBUTED BY: FAMILY DOLLAR SERVICES, INC.,

5093740/0312